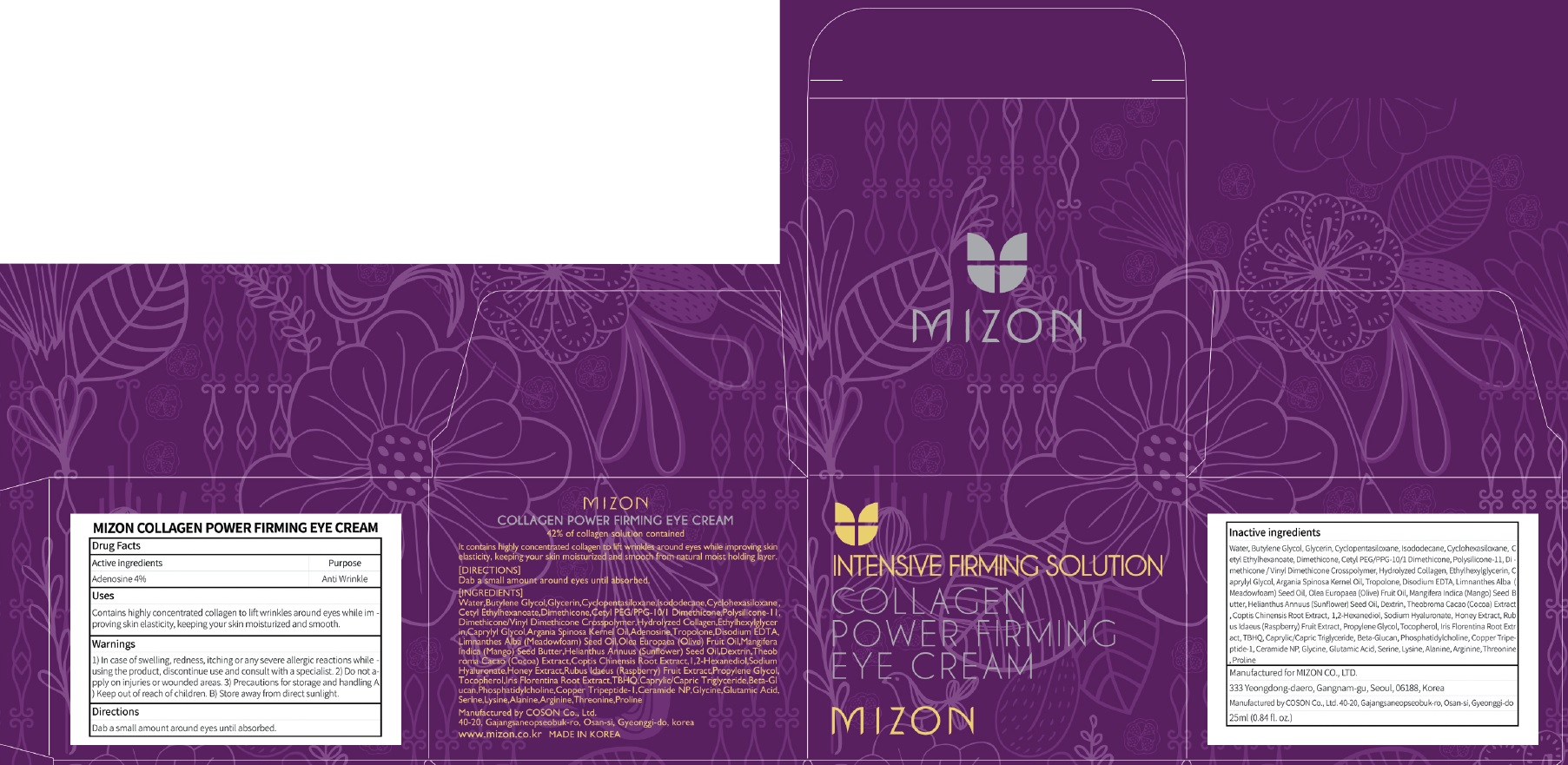 DRUG LABEL: MIZON COLLAGEN POWER FIRMING EYE CREA M
NDC: 57718-260 | Form: CREAM
Manufacturer: MIZON CO.,LTD.
Category: otc | Type: HUMAN OTC DRUG LABEL
Date: 20180724

ACTIVE INGREDIENTS: Adenosine 0.01 g/25 mL
INACTIVE INGREDIENTS: Butylene Glycol; Glycerin

ACTIVE INGREDIENT

Active ingredients: Adenosine 0.04%

INACTIVE INGREDIENT

Inactive ingredients:

Butylene Glycol, Glycerin, Cyclopentasiloxane, Isododecane, Cyclohexasiloxane, Cetyl Ethylhexanoate, Dimethicone, Cetyl PEG/PPG-10/1 Dimethicone, Polysilicone-11, Dimethicone/Vinyl Dimethicone Crosspolymer, Hydrolyzed Collagen, Ethylhexylglycerin, Caprylyl Glycol, Argania Spinosa Kernel Oil, Tropolone, Disodium EDTA, Limnanthes Alba (Meadowfoam) Seed Oil, Olea Europaea (Olive) Fruit Oil, Mangifera Indica (Mango) Seed Butter, Helianthus Annuus (Sunflower) Seed Oil, Dextrin, Theobroma Cacao (Cocoa) Extract, Coptis Chinensis Root Extract, 1,2-Hexanediol, Sodium Hyaluronate, Honey Extract, Rubus Idaeus (Raspberry) Fruit Extract, Propylene Glycol, Tocopherol, Iris Florentina Root Extract, TBHQ, Caprylic/Capric Triglyceride, Beta-Glucan, Phosphatidylcholine, Copper Tripeptide-1, Ceramide NP, Glycine, Glutamic Acid, Serine, Lysine, Alanine, Arginine, Threonine, Proline

PURPOSE

Purpose: Anti Wrinkle

WARNINGS

1) In case of swelling, redness, itching or any severe allergic reactions while using the product, discontinue use and consult with a specialist. 2) Do not apply on injuries or wounded areas. 3) Precautions for storage and handling A) Keep out of reach of children. B) Store away from direct sunlight.

KEEP OUT OF REACH OF CHILDREN

Uses

Contains highly concentrated collagen to lift wrinkles around eyes while improving skin elasticity, keeping your skin moisturized and smooth.

Directions

Dab a small amount around eyes until absorbed.